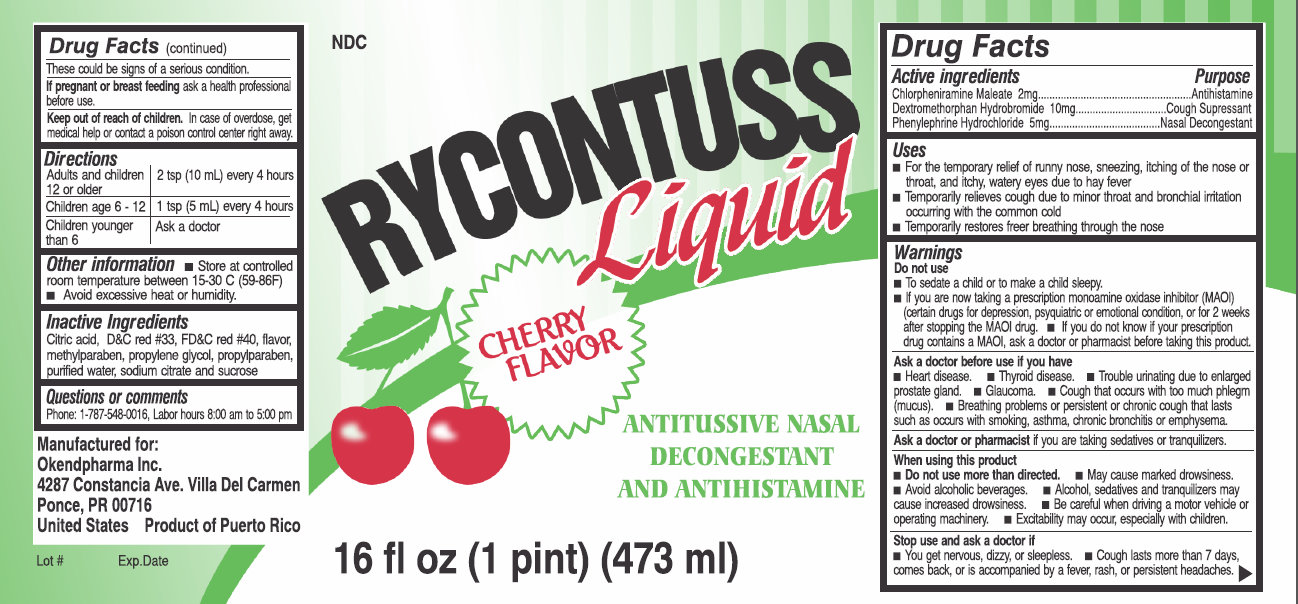 DRUG LABEL: Rycontuss
NDC: 76117-001 | Form: LIQUID
Manufacturer: Okendpharma, Inc.
Category: otc | Type: HUMAN OTC DRUG LABEL
Date: 20241213

ACTIVE INGREDIENTS: CHLORPHENIRAMINE MALEATE 2 mg/5 mL; DEXTROMETHORPHAN HYDROBROMIDE 10 mg/5 mL; PHENYLEPHRINE HYDROCHLORIDE 5 mg/5 mL
INACTIVE INGREDIENTS: CITRIC ACID MONOHYDRATE; D&C RED NO. 33; FD&C RED NO. 40; METHYLPARABEN; PROPYLENE GLYCOL; PROPYLPARABEN; WATER; SODIUM CITRATE; SUCROSE

Rycontuss Liquid Cherry Flavor

Active ingredients Purpose
Chlorpheniramine Maleate 2mg............................................................Antihistamine
Dextromethorphan Hydrobromide 10mg.........................................Cough Supressant
Phenylephrine Hydrochloride 5mg...............................................Nasal Decongestant

PURPOSE

Uses - For the temporary relief of runny nose, sneezing, itching of the nose or throat, and itchy, watery eyes due to hay fever - Temporarily relieves cough due to minor throat and bronchial irritation occurring with the common cold - Temporarily restores freer breathing through the nose

WARNINGS

Warnings Do not use - To sedate a child or to make a child sleepy. - If you are now taking a prescription monoamine oxidase inhibitor (MAOI) (certain drugs for depression, psyquiatric or emotional condition, or for 2 weeks after stopping the MAOI drug. - If you do not know if your prescription drug contains a MAOI, ask a doctor or pharmacist before taking this product.

Ask a doctor before use if you have - Heart disease. - Thyroid disease. - Trouble urinating due to enlarged prostate gland. - Glaucoma. - Cough that occurs with too much phlegm (mucus). - Breathing problems or persistent or chronic cough that lasts such as occurs with smoking, asthma, chronic bronchitis or emphysema.

Ask a doctor or pharmacist if you are taking sedatives or tranquilizers.

When using this product - Do not use more than directed. - May cause marked drowsiness. - Avoid alcoholic beverages. - Alcohol, sedatives and tranquilizers may cause increased drowsiness. - Be careful when driving a motor vehicle or operating machinery. - Excitability may occur, especially with children.

Stop use and ask a doctor if - You get nervous, dizzy, or sleepless. - Cough lasts more than 7 days, come back, or is accompanied by a fever, rash, or persistent headaches. These could be signs of a serious condition. If pregnant or breast feeding ask a health professional before use.

Keep out of reach of children.

INDICATIONS AND USAGE

In case of overdose, get medical help or contact a poison control center right away.

DOSAGE AND ADMINISTRATION

Adults and children 12 or older | 2 tsp (10 mL) every 4 hours
Chidren age 6 - 12 | 1 tsp (5 mL) every 4 hours
Children younger than 6 | Ask a doctor

Other information - Store at controlled room temperature between 15-30 C (58-86F) - Avoid excessive heat or humidity.

Inactive Ingredients
Citric acid, DandC red #33, FDandC red #40, flavor, methylparaben, propylene glycol, propylparaben, purified water, sodium citrate and sucrose.

Questions or comments Phone: 1-787-548-0016, Labor hours 8:00 am to 5:00 pm

DESCRIPTION

Manufactured for: Okendpharma Inc, 4287 Constancia Ave. Villa Del Carmen Ponce, PR 00716 United States Product of Puerto Rico

PACKAGE LABEL

NDC RYCONTUSS Liquid CHERRY FLAVOR ANTITUSSIVE NASAL DECONGESTANT AND ANTIHISTAMINE 16 fl oz (1 print) (473 ml) Lot # Exp.Date